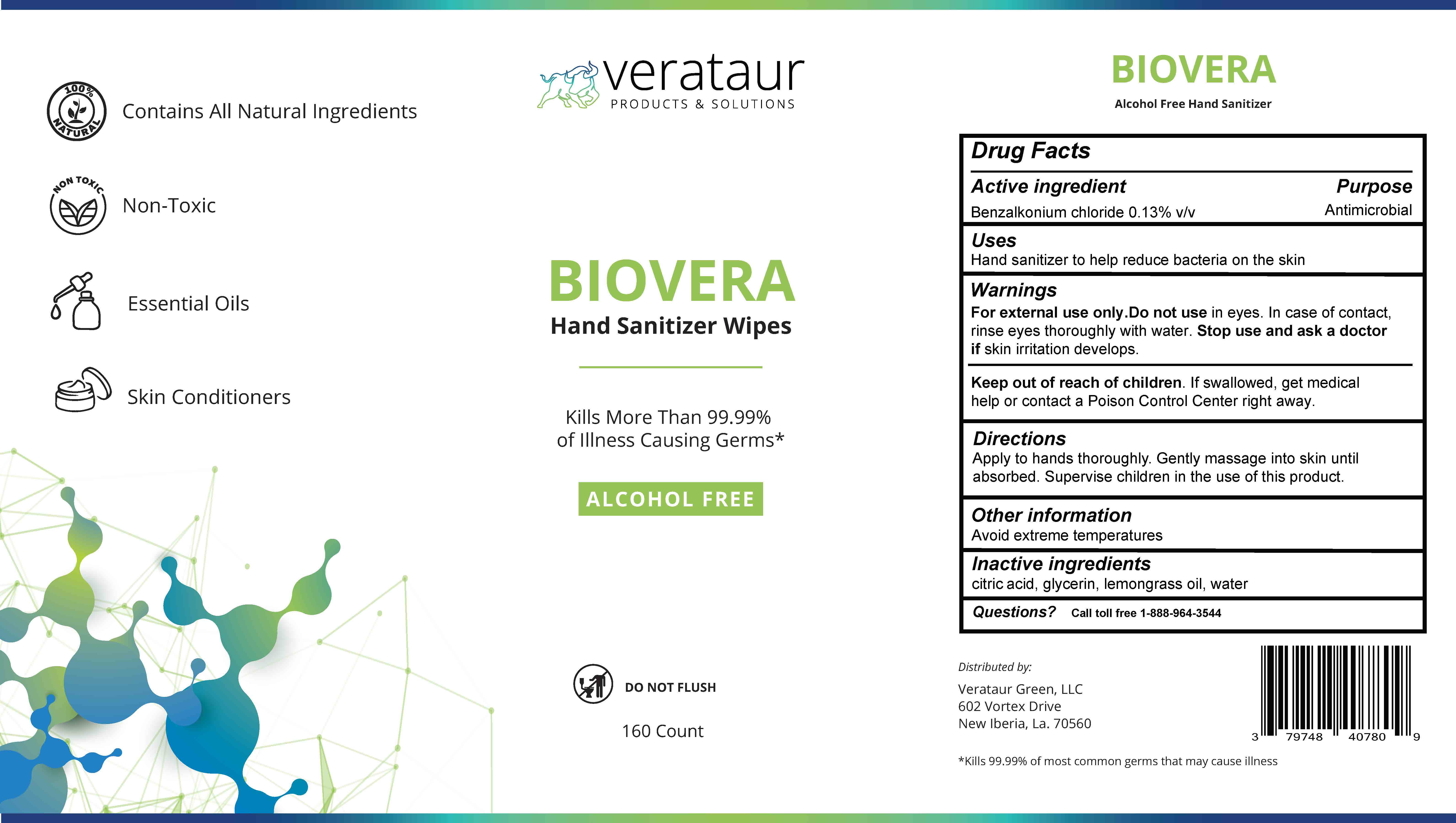 DRUG LABEL: BioVera Hand Sanitizer Wipes
NDC: 79748-407 | Form: LIQUID
Manufacturer: Verataur, LLC.
Category: otc | Type: HUMAN OTC DRUG LABEL
Date: 20200805

ACTIVE INGREDIENTS: BENZALKONIUM CHLORIDE 0.1274 g/100 g
INACTIVE INGREDIENTS: GLYCERIN 0.63 g/100 g; ANHYDROUS CITRIC ACID 0.15 g/100 g; WATER 99.02 g/100 g; EAST INDIAN LEMONGRASS OIL 0.04435 g/100 g

Active ingredient

Benzalkonium chloride 0.13% v/v. Purpose: Antimicrobial

Uses

Hand sanitizer wipes to help reduce bacteria on the skin

Warnings

For external use only. Do not use in eyes. In case of contact, rinse eyes thoroughly with water. Stop use and ask a doctor if skin irritation develops.

Keep out of reach of children.

If swallowed, get medical help or contact a Poison Control Center right away

Directions

Open lid, gently pull out a wipe. Thoroughly wipe as desired. Allow to dry without wiping. Discard wipe in trash after use, do not flush in toilet.

Other Information

Avoid extreme temperatures

Inactive ingredients

citric acid, glycerin, lemongrass oil, water

Questions?

1-888-964-3544, weekdays between 8:00 am and 5:00 pm CST

Purpose

Antiseptic, Hand Sanitizer Wipe